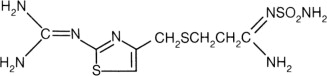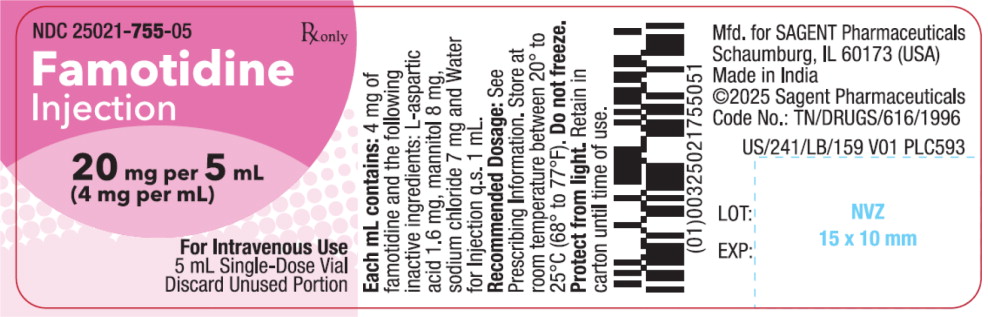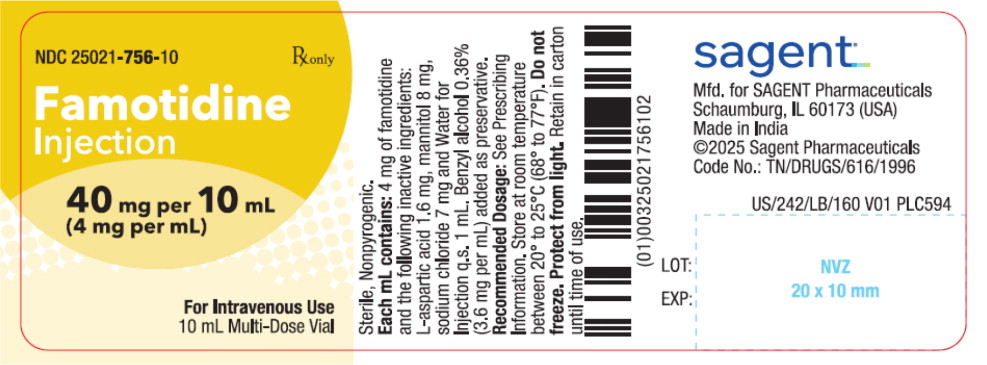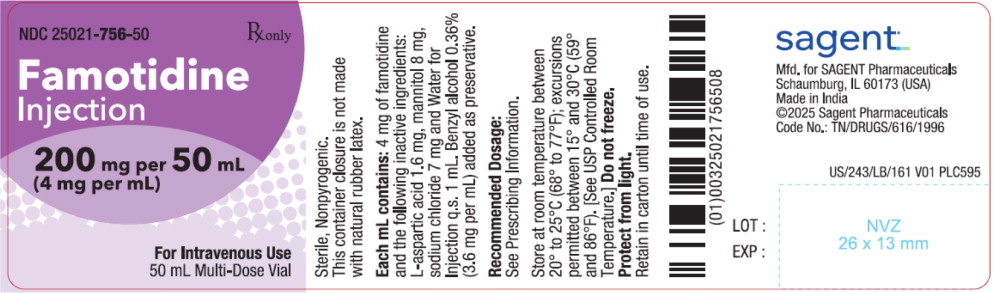 DRUG LABEL: Famotidine
NDC: 25021-755 | Form: INJECTION, SOLUTION
Manufacturer: Sagent Pharmaceuticals
Category: prescription | Type: HUMAN PRESCRIPTION DRUG LABEL
Date: 20251004

ACTIVE INGREDIENTS: Famotidine 4 mg/1 mL
INACTIVE INGREDIENTS: aspartic acid; mannitol; sodium chloride; water; sodium hydroxide

HIGHLIGHTS OF PRESCRIBING INFORMATION

These highlights do not include all the information needed to use FAMOTIDINE INJECTION safely and effectively. See full prescribing information for FAMOTIDINE INJECTION.
FAMOTIDINE injection for intravenous use
Initial U.S. Approval: 1986

1 INDICATIONS AND USAGE

FAMOTIDINE Injection is a histamine-2 (H2) receptor antagonist indicated:

In hospitalized adults, or as an alternative to oral famotidine in adults, for the treatment of:

- active duodenal ulcer (DU).
- active gastric ulcer (GU).
- symptomatic nonerosive gastroesophageal reflux disease (GERD).
- erosive esophagitis due to GERD, diagnosed by endoscopy.
- treatment of pathological hypersecretory conditions (e.g., Zollinger-Ellison syndrome, multiple endocrine neoplasias).
- reduction of the risk of DU recurrence.

In hospitalized pediatric patients 1 year of age and older, or as an alternative to oral famotidine in pediatric patients 1 year of age and older, for the treatment of:

- peptic ulcer disease.

2 DOSAGE AND ADMINISTRATION

Administration Information (2.1)

- Famotidine Injection is intended for use in adult and pediatric hospitalized patients, or as an alternative to oral famotidine.
- Discontinue as soon as the patient is able to tolerate oral treatment and switch to an appropriate oral medication.

Recommended Dosage (2.2)

- Adults: 20 mg every 12 hours.
  - For pathological hypersecretory conditions titrate the dosage to individual patient needs.
- Pediatric Patients 1 year of age and older: 0.25 mg/kg every 12 hours; titrate to a maximum of 0.5 mg/kg every 12 hours (up to maximum of 20 mg every 12 hours) based on clinical response and/or gastric pH determination and endoscopy.
- Administer as an intravenous injection over at least 2 minutes or an intravenous infusion over 15 minutes to 30 minutes.
- Refer to the prescribing information for oral famotidine products for the recommended duration of famotidine treatment.

Renal Impairment (2.3)

- See the full prescribing information for the recommended dosage for adult patients with moderate or severe renal impairment.

3 DOSAGE FORMS AND STRENGTHS

Injection:

- 20 mg/5 mL (4 mg/mL) single-dose vial
- 40 mg/10 mL (4 mg/mL) multi-dose vial
- 200 mg/50 mL (4 mg/mL) multi-dose vial

4 CONTRAINDICATIONS

History of serious hypersensitivity reactions (e.g., anaphylaxis) to famotidine or other H2-receptor antagonists. (4)

5 WARNINGS AND PRECAUTIONS

- Central Nervous System (CNS) Adverse Reactions: Reported in elderly patients and patients with moderate and severe renal impairment; monitor elderly patients for CNS adverse reactions. (5.1, 8.5, 8.6)
- Concurrent GI Malignancy: Absence of GI symptoms does not preclude the presence of gastric malignancy; evaluate prior to initiating therapy. (5.2)
- Risk of Benzyl Alcohol Toxicity in Neonates: Famotidine Injection is not approved in neonates. Serious and fatal adverse reactions have been reported in low-birth weight and preterm neonates who received benzyl-alcohol-containing drugs intravenously. The minimum amount of benzyl alcohol at which these serious adverse reactions may occur is not known. (5.3)

6 ADVERSE REACTIONS

Most common adverse reactions (>1%) are: headache, dizziness, constipation, and diarrhea. (6.1)
To report SUSPECTED ADVERSE REACTIONS, contact Sagent Pharmaceuticals at 1-866-625-1618 or FDA at 1-800-FDA-1088 or www.fda.gov/medwatch.

7 DRUG INTERACTIONS

- Drugs Dependent on Gastric pH for Absorption: Systemic exposure of the concomitant drug may be significantly reduced leading to loss of efficacy. See the prescribing information for other drugs dependent on gastric pH for absorption. (7.1)
- Tizanidine (CYP1A2) Substrate: Potential for substantial increases in blood concentrations of tizanidine resulting in hypotension, bradycardia or excessive drowsiness; avoid concomitant use, if possible. (7.2)

8 USE IN SPECIFIC POPULATIONS

- Renal Impairment: QT prolongation reported in patients with moderate and severe renal impairment. (2.3, 8.6)

FULL PRESCRIBING INFORMATION

1 INDICATIONS AND USAGE

Famotidine Injection is indicated for use in hospitalized adults, or as an alternative to oral famotidine in adults, for the treatment of:

- active duodenal ulcer (DU).
- active gastric ulcer (GU).
- symptomatic nonerosive gastroesophageal reflux disease (GERD).
- erosive esophagitis due to GERD, diagnosed by endoscopy.
- treatment of pathological hypersecretory conditions (e.g., Zollinger-Ellison syndrome, multiple endocrine neoplasias).
- reduction of the risk of duodenal ulcer recurrence.

Pediatric Patients 1 Year of Age and Older

Famotidine Injection is indicated in hospitalized pediatric patients 1 year of age and older, or as an alternative to oral famotidine in pediatric patients 1 year of age and older, for the treatment of peptic ulcer disease.

2 DOSAGE AND ADMINISTRATION

2.1 Important Administration Information

- Famotidine Injection is intended for use in adult and pediatric hospitalized patients, or as an alternative to oral famotidine.
- Discontinue Famotidine Injection as soon as the patient is able to tolerate oral treatment and switch to an appropriate oral medication.

2.2 Recommended Dosage in Adults and Pediatric Patients 1 Year of Age and Older

The recommended dosage of Famotidine Injection in adults and pediatric patients 1 year of age and older is shown in Tables 1 and 2, respectively.

Administer Famotidine Injection as an intravenous injection over at least 2 minutes or as an intravenous infusion over 15 minutes to 30 minutes [see Dosage and Administration (2.4)].

Refer to the prescribing information for oral famotidine products for the recommended duration of famotidine treatment.

Table 1. Recommended Dosage^1 of Famotidine Injection in Adults
Indication | Recommended Dosage
Active Duodenal Ulcer | 20 mg every 12 hours
Active Gastric Ulcer | 20 mg every 12 hours
Symptomatic Nonerosive GERD | 20 mg every 12 hours
Erosive Esophagitis Diagnosed by Endoscopy | 20 mg every 12 hours
Reduction of the Risk of Duodenal Ulcer Recurrence | 20 mg every 12 hours
Pathological Hypersecretory Conditions | Starting dosage is 20 mg every 12 hours; titrate the dosage to individual patient needs
^1 Refer to the prescribing information for oral famotidine products for the recommended duration of famotidine treatment.

Table 2. Recommended Dosage^1 of Famotidine Injection in Pediatric Patients 1 Year of Age and Older
Indication | Recommended Dosage
Peptic Ulcer Disease | - 0.25 mg/kg every 12 hours (maximum 20 mg every 12 hours) - Titrate to a maximum dosage of 0.5 mg/kg every 12 hours (maximum of 20 mg every 12 hours) based on clinical response and/or gastric pH determination and endoscopy.
^1 Refer to the prescribing information for oral famotidine products for the recommended duration of famotidine treatment.

2.3 Recommended Dosage in Patients with Renal Impairment

Adults

The recommended dosage for adult patients with moderate to severe renal impairment is shown in Table 3. Administer Famotidine Injection as an intravenous injection over at least 2 minutes or as an intravenous infusion over 15 minutes to 30 minutes [see Dosage and Administration (2.4)].

Table 3. Recommended Dosage^1 of Famotidine Injection in Adults with Renal Impairment
Indication | Recommended Dosage
Indication | Creatinine Clearance 30 to 60 mL/minute | Creatinine Clearance less than 30 mL/minute
Active Duodenal Ulcer | 20 mg once daily | 10 mg once daily
Active Gastric Ulcer | 20 mg once daily | 10 mg once daily
Symptomatic Nonerosive GERD | 20 mg once daily | 10 mg once daily
Erosive Esophagitis Diagnosed by Endoscopy | 20 mg once daily | 10 mg once daily
Reduction of the Risk of Duodenal Ulcer Recurrence | 20 mg once daily | 10 mg once daily
Pathological Hypersecretory Conditions | Avoid use^2 | Avoid use^2
^1 Refer to the prescribing information for oral famotidine products for the recommended duration of famotidine treatment.
^2 The dosage required to treat pathological hypersecretory conditions may exceed the maximum doses evaluated in patients with impaired renal function. The risk for increased adverse reactions in renally impaired patients treated with Famotidine Injection for pathological hypersecretory conditions is unknown.

Pediatric Patients

A safe and effective dosage has not been established in pediatric patients with renal impairment 1 year of age and older for the treatment of peptic ulcer disease [see Use in Specific Populations (8.6)].

2.4 Preparation and Administration Instructions

Intravenous Injection over at least 2 Minutes

- Aseptically withdraw the required volume from the vial. Do not dilute.

Intravenous Infusion over 15 Minutes to 30 Minutes

1. Aseptically dilute the required dose of Famotidine Injection in 100 mL of one of the following solutions:
  - 5% Dextrose for Injection
  - 0.9% Sodium Chloride Injection
  - 10% Dextrose for Injection
  - Lactated Ringer's Injection
2. Gently invert the bag 4 to 5 times. Avoid shaking.
3. Before administration, inspect the bag for particulate matter and discoloration. Discard the bag if particulate and/or discoloration are observed.

Storage of Diluted Product:

Use the diluted product immediately. Alternatively, refrigerate between 2° and 8°C (36° and 46°F) and use within 48 hours.

3 DOSAGE FORMS AND STRENGTHS

Injection: a clear, colorless, solution supplied ready-to-use as:

- 20 mg/5 mL (4 mg/mL) single-dose vial
- 40 mg/10 mL (4 mg/mL) multi-dose vial
- 200 mg/50 mL (4 mg/mL) multi-dose vial

4 CONTRAINDICATIONS

Famotidine Injection is contraindicated in patients with a history of serious hypersensitivity reactions (e.g., anaphylaxis) to famotidine or other H2-receptor antagonists.

5 WARNINGS AND PRECAUTIONS

5.1 Central Nervous System Adverse Reactions

Central nervous system (CNS) adverse reactions, including confusion, delirium, hallucinations, disorientation, agitation, seizures, and lethargy, have been reported in elderly patients and patients with moderate and severe renal impairment treated with famotidine. Monitor elderly patients for CNS adverse reactions [see Use in Specific Populations (8.5)]. Dosage adjustments are recommended in adult patients with moderate and severe renal impairment due to higher famotidine systemic exposure compared to patients with normal renal function [see Dosage and Administration (2.3), Use in Specific Populations (8.6), and Clinical Pharmacology (12.3)].

5.2 Concurrent Gastric Malignancy

In adults, symptomatic response to therapy with Famotidine Injection does not preclude the presence of gastric malignancy. Consider evaluation for gastric malignancy in adult patients who have a suboptimal response or an early symptomatic relapse after completing treatment with Famotidine Injection.

5.3 Risk of Benzyl Alcohol Toxicity in Neonates

Famotidine Injection is not approved in neonates. Serious adverse reactions, including fatal reactions, of new onset or worsening metabolic acidosis that progressed to neurotoxicity, and in some cases gasping syndrome, have been reported in low-birth weight neonates (less than 2,500 grams) and preterm neonates (gestational age less than 34 weeks) who received benzyl alcohol (BA)-containing drugs intravenously. Gasping syndrome is a life-threatening condition in neonates caused by BA toxicity and is primarily characterized by multiorgan dysfunction secondary to metabolic acidosis, which leads to gasping respirations and death. The minimum amount of BA at which these serious adverse reactions, including fatal reactions, may occur is not known (Famotidine Injection contains 3.6 mg of BA per mL) [see Use in Specific Populations (8.4)].

6 ADVERSE REACTIONS

6.1 Clinical Trials Experience

Because clinical trials are conducted under widely varying conditions, adverse reaction rates observed in the clinical trials of a drug cannot be directly compared to rates in the clinical trials of another drug and may not reflect the rates observed in practice.

The safety of Famotidine Injection has been established based on adequate and well-controlled studies of an oral famotidine product. The following is a summary of the adverse reactions reported in those studies.

Oral famotidine was studied in 7 U.S. and international placebo- and active-controlled trials in approximately 2,500 patients. A total of 1,442 patients were treated with oral famotidine, including 302 treated with 40 mg twice daily, 456 treated with 20 mg twice daily, 461 treated with 40 mg once daily, and 396 treated with 20 mg once daily. The population was 17 to 91 years old, fairly well distributed between sex and race; however, the predominant race was White.

Adverse reactions reported in ≥1% of patients treated with oral famotidine in clinical trials were: headache, dizziness, constipation, and diarrhea.

The following other adverse reactions were reported in less than 1% of patients treated with oral famotidine in clinical trials:

Body as a Whole: fever, asthenia, fatigue

Cardiovascular: palpitations

Gastrointestinal: cholestatic jaundice, elevated liver enzymes, vomiting, nausea, abdominal discomfort, anorexia, dry mouth

Hematologic: thrombocytopenia

Hypersensitivity: orbital edema, rash, conjunctival injection, bronchospasm

Musculoskeletal: musculoskeletal pain, arthralgia

Nervous System/Psychiatric: seizure, hallucinations, depression, anxiety, decreased libido, insomnia, somnolence

Respiratory: interstitial pneumonia

Skin: pruritus, dry skin, flushing

Special Senses: tinnitus, taste disorder

Other: impotence

Adverse reactions reported with oral famotidine may also occur with Famotidine Injection. In addition, transient irritation at the injection site was reported with intravenous famotidine.

6.2 Postmarketing Experience

The following adverse reactions have been identified during post-approval use of famotidine. Because these reactions are reported voluntarily from a population of uncertain size, it is not always possible to reliably estimate their frequency or establish a causal relationship to drug exposure.

Cardiovascular: arrhythmia, AV block, prolonged QT interval

Gastrointestinal: cholestatic jaundice, hepatitis

Hematologic: agranulocytosis, pancytopenia, leukopenia

Hypersensitivity: anaphylaxis, angioedema, facial edema, urticaria

Musculoskeletal: rhabdomyolysis, muscle cramps

Nervous System/Psychiatric: confusion, agitation, paresthesia

Respiratory: interstitial pneumonia

Skin: toxic epidermal necrolysis/Stevens-Johnson syndrome

7 DRUG INTERACTIONS

7.1 Drugs Dependent on Gastric pH for Absorption

Famotidine can reduce the absorption of other drugs due to its effect on reducing intragastric acidity, leading to loss of efficacy of the concomitant drug. See the prescribing information for other drugs dependent on gastric pH for absorption.

7.2 Tizanidine (CYP1A2 Substrate)

Although not studied clinically, famotidine is considered a weak CYP1A2 inhibitor and may lead to substantial increases in blood concentrations of tizanidine, a CYP1A2 substrate. Avoid concomitant use with Famotidine Injection. If concomitant use is necessary, monitor for hypotension, bradycardia or excessive drowsiness. Refer to the full prescribing information for tizanidine.

8 USE IN SPECIFIC POPULATIONS

8.1 Pregnancy

Risk Summary

Available data with H2-receptor antagonists, including famotidine, in pregnant women over decades of use have not identified a drug-associated risk of major birth defects, miscarriage or adverse maternal or fetal outcomes. Reproductive studies have been performed in rats and rabbits at intravenous doses of up to 200 mg/kg/day, with no obvious adverse developmental effects (see Data). Famotidine Injection contains benzyl alcohol as a preservative [see How Supplied/Storage and Handling (16)]. Because benzyl alcohol is rapidly metabolized by a pregnant female, benzyl alcohol exposure in the fetus is unlikely.

The background risk for major birth defects and miscarriage for the indicated population is unknown. All pregnancies have a background risk of birth defect, loss, or other adverse outcomes. In the U.S. general population, the background risk of major birth defects and miscarriage in clinically recognized pregnancies is 2% to 4% and 15% to 20%, respectively.

Data

Animal Data

Reproductive studies have been performed in rats and rabbits at oral doses of up to 2,000 and 500 mg/kg/day, respectively, and in both species at intravenous doses of up to 200 mg/kg/day and have revealed no significant evidence of impaired fertility or harm to the fetus due to famotidine.

8.2 Lactation

Risk Summary

There are limited data available on the presence of famotidine in human breast milk following oral administration. There were no effects on the breastfed infant. There are no data on famotidine effects on milk production. Famotidine Injection contains benzyl alcohol as a preservative. Because benzyl alcohol is rapidly metabolized by a lactating female, benzyl alcohol exposure in the breastfed neonate is unlikely.

The developmental and health benefits of breastfeeding should be considered along with the mother's clinical need for Famotidine Injection and any potential adverse effects on the breastfed child from famotidine or from the underlying maternal condition.

8.4 Pediatric Use

Peptic Ulcer Disease

The safety and effectiveness of Famotidine Injection have been established in pediatric patients 1 year to less than 17 years of age for the treatment of peptic ulcer disease in hospitalized patients or as an alternative to oral famotidine. Use of Famotidine Injection in this age group is supported by evidence from adequate and well-controlled studies of oral famotidine in adults with additional pharmacokinetic and pharmacodynamic data in pediatric patients 1 year to less than 17 years of age [see Dosage and Administration (2.2) and Clinical Pharmacology (12.2, 12.3)].

A safe and effective dosage has not been established in pediatric patients 1 year to less than 17 years of age with renal impairment for the treatment of peptic ulcer disease.

The safety and effectiveness of Famotidine Injection for the treatment of peptic ulcer disease in pediatric patients less than 1 year of age have not been established.

Other Conditions

The safety and effectiveness of Famotidine Injection for the treatment of symptomatic nonerosive GERD, erosive esophagitis due to GERD, pathological hypersecretory conditions and reduction of the risk of DU recurrence have not been established in pediatric patients.

Risk of Benzyl Alcohol Toxicity in Neonates

Famotidine Injection is not approved for use in neonates. Serious adverse reactions, including fatal reactions, of new onset or worsening metabolic acidosis that progressed to neurotoxicity, and in some cases gasping syndrome, have been reported in low-birth weight neonates and preterm neonates who received benzyl alcohol (BA)-containing drugs intravenously. Gasping syndrome is a life-threatening condition in neonates caused by BA toxicity that is characterized by new onset or worsening metabolic acidosis with gradual neurological deterioration, seizures, intracranial hemorrhage, hematologic abnormalities, skin breakdown, hepatic and kidney failure, hypotension, bradycardia, and gasping respirations followed by death. In reported cases, BA in amounts of 99 to 234 mg/kg/day produced blood BA levels of 6.6 to 14.9 mg/dL, but the minimum amount of BA at which gasping syndrome may occur in neonates is not known (Famotidine Injection contains 3.6 mg of BA per mL) [see Warnings and Precautions (5.3)].

8.5 Geriatric Use

Of the 1,442 patients treated with oral famotidine in clinical studies, approximately 10% were 65 and older. In these studies, no overall differences in safety or effectiveness were observed between elderly and younger patients. In elderly patients, there are no clinically significant age-related changes in the pharmacokinetics of famotidine [see Clinical Pharmacology (12.3)].

In postmarketing experience, CNS adverse reactions have been reported in elderly patients with and without renal impairment receiving famotidine. Monitor elderly patients for CNS adverse reactions [see Warnings and Precautions (5.1)]. Famotidine is known to be substantially excreted by the kidney, and the risk of adverse reactions to Famotidine Injection may be greater in elderly patients, particularly those with impaired renal function [see Dosage and Administration (2.3) and Use in Specific Populations (8.6)].

8.6 Renal Impairment

CNS adverse reactions and prolonged QT intervals have been reported in patients with moderate and severe renal impairment [see Warnings and Precautions (5.1)]. The clearance of famotidine is reduced in adults with moderate and severe renal impairment compared to adults with normal renal function [see Clinical Pharmacology (12.3)]. The recommended dosage in adults with moderate or severe renal impairment (creatinine clearance <60 mL/minutes) is less than the recommended dosage in adults with normal renal function [see Dosage and Administration (2.3)]. The recommended dosage in adults with mild renal impairment (creatinine clearance ≥60 mL/minute) is the same as the recommended dosage in adults with normal renal function.

Data are not available to establish a safe and effective dosage in pediatric patients 1 year to less than 17 years of age with renal impairment for the treatment of peptic ulcer disease.

10 OVERDOSAGE

Adverse reactions reported in cases of overdosage are similar to the adverse reactions reported with use of the recommended dosage [see Adverse Reactions (6)]. In the event of overdosage, treatment should be symptomatic and supportive. In the event of overdosage, monitor the patient, and employ supportive therapy. Due to low binding to plasma proteins, famotidine is eliminated by hemodialysis. There is limited experience on the usefulness of hemodialysis as a treatment for famotidine overdosage.

Consider contacting the Poison Help line (1-800-222-1222) or a medical toxicologist for additional overdose management recommendations.

11 DESCRIPTION

The active ingredient in Famotidine Injection is a histamine H2-receptor antagonist.

Famotidine, USP is N'-(aminosulfonyl)-3-[[[2-[ (diaminomethylene)amino ]-4 thiazolyl]methyl]thio]propanimidamide. The empirical formula of famotidine is C8H15N7O2S3 and its molecular weight is 337.45. Its structural formula is:

Famotidine, USP is a white to pale yellow crystalline compound that is freely soluble in glacial acetic acid, slightly soluble in methanol, very slightly soluble in water, and practically insoluble in ethanol.

Famotidine Injection is supplied as a premixed, ready-to-use, sterile solution for intravenous injection. Each mL contains 4 mg of famotidine and the following inactive ingredients: L-aspartic acid 1.6 mg, mannitol 8 mg, sodium chloride 7 mg, and Water for Injection q.s. 1 mL. The multiple-dose vials of 10 mL and 50 mL also contain benzyl alcohol 0.36% (3.6 mg per mL) added as a preservative. The pH ranges for all three concentrations range from 5.7 to 6.4 and may have been adjusted with sodium hydroxide.

12 CLINICAL PHARMACOLOGY

12.1 Mechanism of Action

Famotidine is a competitive inhibitor of histamine H2-receptors. The primary clinically important pharmacologic activity of famotidine is inhibition of gastric secretion. Both the acid concentration and volume of gastric secretion are suppressed by famotidine, while changes in pepsin secretion are proportional to volume output.

12.2 Pharmacodynamics

Adults

Famotidine inhibited basal and nocturnal gastric secretion, as well as secretion stimulated by food and pentagastrin. After intravenous administration, the maximum effect was achieved within 30 minutes. Single intravenous doses of 20 mg inhibited nocturnal secretion for a period of 10 to 12 hours.

Famotidine had little or no effect on fasting or postprandial serum gastrin levels. Gastric emptying and exocrine pancreatic function were not affected by famotidine.

In clinical pharmacology studies, systemic effects of famotidine in the central nervous system (CNS), cardiovascular, respiratory or endocrine systems were not noted. Also, no antiandrogenic effects were noted. Serum hormone levels, including prolactin, cortisol, thyroxine (T4), and testosterone, were not altered after treatment with famotidine.

Pediatric Patients

Pharmacodynamics of famotidine were evaluated in five pediatric patients 2 to 13 years of age using the sigmoid Emax model. These data suggest that the relationship between serum concentration of famotidine and gastric acid suppression is similar to that observed in one study of adults (Table 4).

Table 4: Pharmacodynamics of Famotidine Using the Sigmoid Emax Model
 | EC50(ng/mL) a
Pediatric Patients | 26 ± 13
Data from one study
a) Healthy adult subjects | 26.5 ± 10.3
b) Adult patients with upper GI bleeding | 18.7 ± 10.8
a Using the sigmoid Emax model, serum concentration of famotidine associated with 50% maximum gastric acid reduction. Values are presented as means ± SD

Five published studies (Table 5) examined the effect of famotidine on gastric pH and duration of acid suppression in pediatric patients. While each study had a different design, acid suppression data over time are summarized as follows:

Table 5: Effect of Intravenous Famotidine on Gastric pH and Duration of Acid Suppression in Pediatric Patients 1 to 15 Years of Age
Dosage Regimen | Number of Patients | Effect on Gastric Acida | Patient Age Range
0.3 mg/kg, single-dose | 6 | gastric pH >3.5 for 8.7 ± 4.7b hours | 2 to 7 years
0.5 mg/kg, single-dose | 9 | a >2 pH unit increase above baseline ingastric pH for >8 hours | 2 to 13 years
0.5 mg/kg twice daily | 4 | gastric pH >5 for 13.5 ± 1.8b hours | 6 to 15 years
a Values reported in published literature
b Means ± SD
c Mean (95% confidence interval)

12.3 Pharmacokinetics

Plasma levels after multiple doses are similar to those after single doses.

Distribution

Fifteen to 20% of famotidine in plasma is protein bound.

Elimination

Metabolism

Famotidine undergoes minimal first-pass metabolism. Sixty-five to 70% of an intravenous dose are recovered in the urine as unchanged compound. The only metabolite identified in humans is the S-oxide.

Excretion

Famotidine has an elimination half-life of 2.5 to 3.5 hours. Famotidine is eliminated by renal (65 to 70%) and metabolic (30 to 35%) routes. Renal clearance is 250 to 450 mL/minutes, indicating some tubular excretion.

Specific Populations

Pediatric Patients

Table 6 presents pharmacokinetic data for famotidine administered intravenously. Areas under the curve (AUCs) are normalized to a 0.5 mg/kg intravenous dose for pediatric patients 1 to 15 years of age and compared with an extrapolated 40 mg intravenous dose in adults. Extrapolation is based on results obtained with a 20 mg intravenous adult dose). The pharmacokinetic parameters for pediatric patients, aged 1 year to 15 years, are comparable to those obtained for adults.

Table 6: Pharmacokinetic Parametersa of Intravenous Famotidine In Pediatric Patients 1 Year to 15 Years of Age and Adults
Age (N=number of patients) | Area Under the Curve (AUC) (ng-hr/mL) | Total Clearance (Cl) (L/hr/kg) | Volume of Distribution (Vd) (L/kg) | Elimination Half-Life (T 1/2) (hours)
1 to 11 years (N=20) | 1089 ± 834 | 0.54 ± 0.34 | 2.07 ± 1.49 | 3.38 ± 2.6
11 to 15 years (N=6) | 1140 ± 320 | 0.48 ± 0.14 | 1.5 ± 0.4 | 2.3 ± 0.4
Adults (N=16) | 1726b | 0.39 ± 0.14 | 1.3 ± 0.2 | 2.83 ± 0.99
a Values are presented as means ± SD unless indicated otherwise
b Mean value only
c Single center study
d Multicenter study

Geriatric Patients

In elderly patients, there are no clinically significant age-related changes in the pharmacokinetics of famotidine. However, in elderly patients with decreased renal function, the clearance of the drug may be decreased [see Use in Specific Populations (8.5)].

Patients with Renal Impairment

In adult patients with severe renal impairment (creatinine clearance less than 30 mL/min), the systemic exposure (AUC) of famotidine increased at least 5-fold. In adult patients with moderate renal impairment (creatinine clearance between 30 to 60 mL/minute), the AUC of famotidine increased at least 2-fold [see Dosage and Administration (2.3) and Use in Specific Populations (8.6)].

Drug Interaction Studies

Human Organic Anion Transporter (OAT) 1 and 3

In vitro studies indicate that famotidine is a substrate for OAT1 and OAT3. Following coadministration of probenecid (1500 mg), an inhibitor of OAT1 and OAT3, with a single oral 20 mg dose of famotidine in eight healthy subjects, the serum AUC0-10h of famotidine increased from 424 to 768 ng•hr/mL and the maximum serum concentration (Cmax) increased from 73 to 113 ng/mL. Renal clearance, urinary excretion rate and amount of famotidine excreted unchanged in urine were decreased. The clinical relevance of this interaction is unknown.

Multidrug and Toxin Extrusion Protein 1 (MATE-1)

An in vitro study showed that famotidine is an inhibitor of MATE-1. However, no clinically significant interaction with metformin, a substrate for MATE-1, was observed.

CYP1A2

Famotidine is a weak CYP1A2 inhibitor [see Drug Interaction (7.2)]

13 NONCLINICAL TOXICOLOGY

13.1 Carcinogenesis, Mutagenesis, Impairment of Fertility

The carcinogenic potential of intravenously administered famotidine has not been determined. In a 106-week study in rats and a 92-week study in mice given oral doses of up to 2,000 mg/kg/day there was no evidence of carcinogenic potential for famotidine.

Famotidine was negative in the bacterial mutagen test (Ames test) using Salmonella typhimurium and Escherichia coli with or without rat liver enzyme activation at concentrations up to 10,000 mcg/plate. In in vivo studies in mice, with a micronucleus test and a chromosomal aberration test, no evidence of a mutagenic effect was observed.

In studies with rats given oral doses of up to 2,000 mg/kg/day or intravenous doses of up to 200 mg/kg/day, fertility and reproductive performance were not affected.

16 HOW SUPPLIED/STORAGE AND HANDLING

Famotidine Injection is a clear, colorless, sterile solution supplied premixed and ready-to-use as follows:

 | Famotidine Injection (Preservative-free)
NDC | (4 mg per mL) | Package Factor
25021-755-05 | 20 mg per 5 mL Single-Dose Vial | 25 vials per carton
 | Famotidine Injection (Preservative)
NDC | (4 mg per mL) | Package Factor
25021-756-10 | 40 mg per 10 mL Multi-Dose Vial | 10 vials per carton
25021-756-50 | 200 mg per 50 mL Multi-Dose Vial | 1 vial per carton

Storage Conditions

Store at room temperature between 20° to 25°C (68° to 77°F); excursions permitted between 15° and 30°C (59° and 86°F). [See USP Controlled Room Temperature.]

If not used immediately, store diluted solutions of Famotidine Injection between 2° and 8°C (36° and 46°F) for up to 48 hours [see Dosage and Administration (2.4)].

Do not freeze.
Protect from light. Retain in carton until time of use.

The container closure is not made with natural rubber latex.

17 PATIENT COUNSELING INFORMATION

Central Nervous System (CNS) Adverse Reactions

Advise elderly patients and those with moderate and severe renal impairment of the risk of CNS adverse reactions, including confusion, delirium, hallucinations, disorientation, agitation, seizures, and lethargy [see Warnings and Precautions (5.1)]. Report symptoms immediately to a healthcare provider.

QT Interval Prolongation

Advise patients with moderate and severe renal impairment of the risk of QT interval prolongation [see Use in Specific Populations (8.6)]. Report new cardiac symptoms, such as palpitations, fainting and dizziness or lightheadedness, immediately to a healthcare provider.

Risk of Benzyl Alcohol Toxicity in Neonates

Inform caregivers that serious adverse reactions, including fatal reactions, have been reported in neonates who received drugs containing benzyl alcohol intravenously. Inform the healthcare provider if neurologic, hematologic or cardiac adverse reactions occur [see Warnings and Precautions (5.3)].

sagent®
Mfd. for SAGENT Pharmaceuticals
Schaumburg, IL 60173 (USA)
Made in India
©2025 Sagent Pharmaceuticals

PACKAGE LABEL – PRINCIPAL DISPLAY PANEL – Vial Label

NDC 25021-755-05

Rx only

Famotidine Injection

20 mg per 5 mL

(4 mg per mL)

For Intravenous Use

5 mL Single-Dose Vial

Discard Unused Portion

PACKAGE LABEL – PRINCIPAL DISPLAY PANEL – Vial Label

NDC 25021-756-10

Rx only

Famotidine Injection

40 mg per 10 mL

(4 mg per mL)

For Intravenous Use

10 mL Multi-Dose Vial

PACKAGE LABEL – PRINCIPAL DISPLAY PANEL – Vial Label

NDC 25021-756-50

Rx only

Famotidine Injection

200 mg per 50 mL

(4 mg per mL)

For Intravenous Use

50 mL Multi-Dose Vial